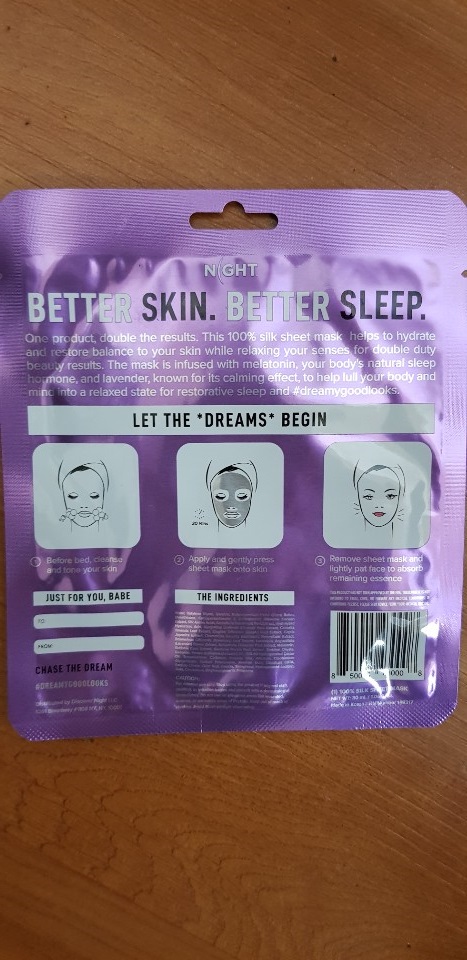 DRUG LABEL: MELATONIN SHEET MASK
NDC: 70812-004 | Form: LIQUID
Manufacturer: BIOSTECH CO., LTD.
Category: otc | Type: HUMAN OTC DRUG LABEL
Date: 20201008

ACTIVE INGREDIENTS: GLYCERIN 5 g/100 mL
INACTIVE INGREDIENTS: WATER; BUTYLENE GLYCOL; ALLANTOIN; DIMETHICONE

ACTIVE INGREDIENT

glycerin

INACTIVE INGREDIENT

Water, Aqua
Scutellaria Baicalensis Root Extract
Butylene Glycol
Cyclomethicone
Dimethicone
Butyrospermum Parkii (Shea) Butter
Silkworm Cocoon Extract
Beeswax
Persea Gratissima (Avocado) Oil
Cetearyl Olivate
Sorbitan Olivate
Melatonin
PEG-60 Hydrogenated Castor Oil
Carbomer
Triethanolamine
Sodium Citrate
Hydrolyzed Collagen
Allantoin
Glycyrrhiza Glabra (Licorice) Root Extract
Zingiber Officinale (Ginger) Root Extract
Schizandra Chinensis Fruit Extract
Coptis japonica Extract
Camellia Sinensis Leaf Extract
Propolis Wax
Asiaticoside
Carrylyl glycol
Citric Acid
Sodium Polyacrylate
Dipotassium Glycyrrhizate
Xanthan Gum
Polyquaternium-51
Disodium EDTA
Gold(1ppm)
Lavandula Angustifolia (Lavender) Oil
Cananga Odorata Leaf Oil

PURPOSE

helps to hydrate and restore balance to your skin

keep out of reach of the children

INDICATIONS AND USAGE

before bed, cleanse and tone your skin

apply and gently pross sheet mask onto skin

remove sheet mask and lightly pat face to absorb remaining essence

WARNINGS

For external use only.
Do not use in the eyes. In case of contact, rinse eyes thoroughly with water.

DOSAGE AND ADMINISTRATION

for external use only